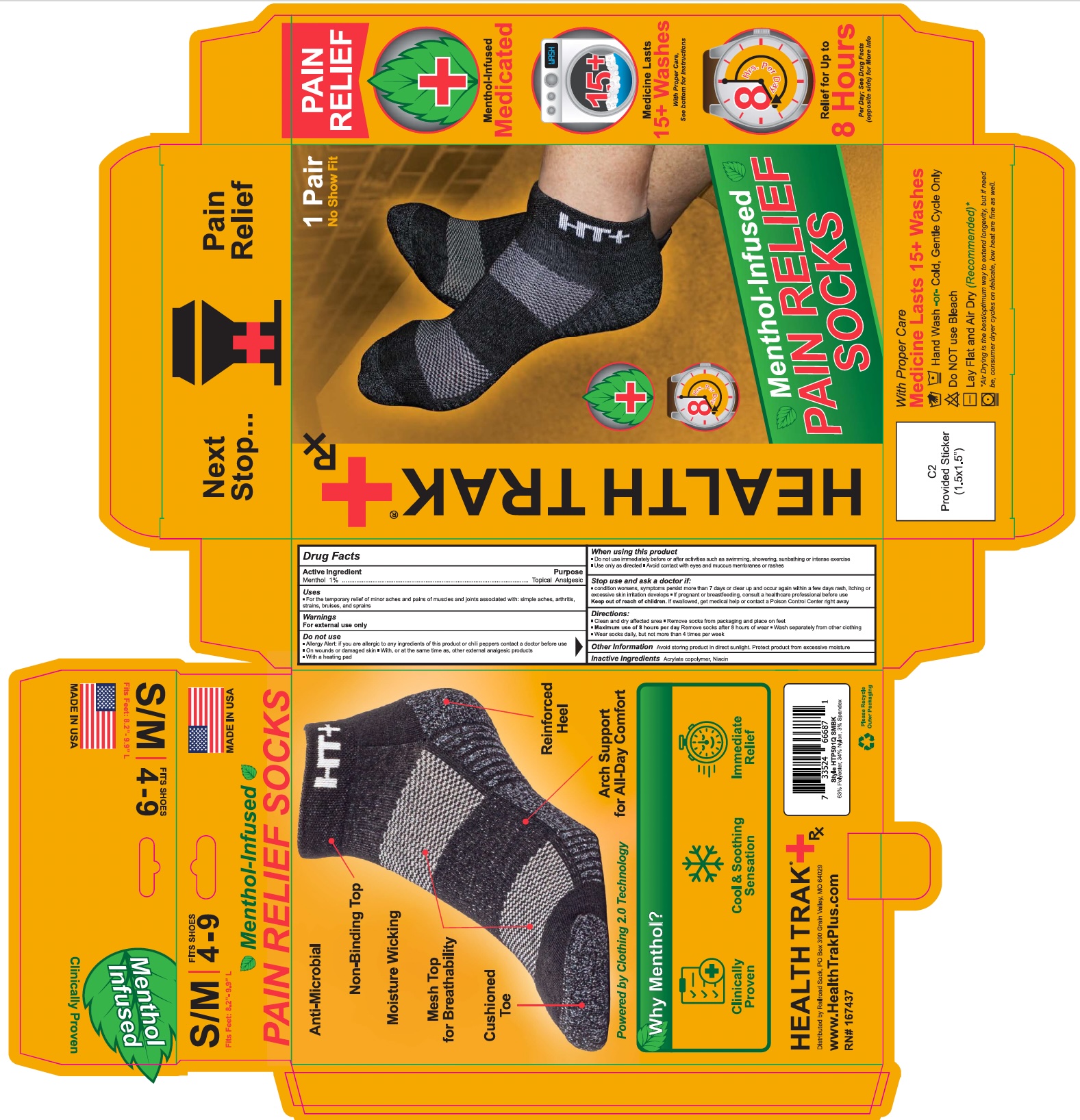 DRUG LABEL: Health Trak Plus Menthol-Infused Pain Relief Socks
NDC: 85720-8131 | Form: CLOTH
Manufacturer: Railroad Sock LLC
Category: otc | Type: HUMAN OTC DRUG LABEL
Date: 20251218

ACTIVE INGREDIENTS: MENTHOL 1 g/100 g
INACTIVE INGREDIENTS: NIACIN; BUTYL ACRYLATE/METHYL METHACRYLATE/METHACRYLIC ACID COPOLYMER (18000 MW)

85720-8131 Railroad Sock Menthol Infused Pain Relief Socks

Active Ingredient

Menthol 1%

Purpose

Topical Analgesic

Uses

For the temporary relief of minor aches and pains of muscles and joints associated with: simple aches, arthritis, strains, bruises and sprains.

Warnings

For external use only.

Do not use

- Allergy Alert: If you are allergic to any ingredients of this product or chilli peppers contact a doctor before use
- On wounds or damagend skin
- With or at the same time as other external analgesic products
- With a heating pad

When using this product

- Do not use immediately before or after activities such as swimming, showering, sunbathing or intense exercise.
- Use only as directed.
- Avoid contact with eyes and muscous membranes or rashes.

Stop use and ask a doctor if

- condition worsens, symptoms persist more than 7 days or clear up and occur again within a few days
- rash, itching or excessive skin irritation develops

If pregnant or breastfeeding

Consult a healthcare professional before use.

Keep out of reach of children

If swallowed, get medical help or contact a Poison Control Center right away.

Directions

- Clean and dry affected area
- Remove socks from packaging and place on feet
- Maximum use of 8 hours per day, remove socks after 8 hours of wear
- Wash separately from other clothing
- Wear socks daily but nore more than 4 times per week

Other Information

- Avoid storing product in direct sunlight.
- Protect product from excessive moisture.

Inactive ingredients

Acrylate copolymer, niacin